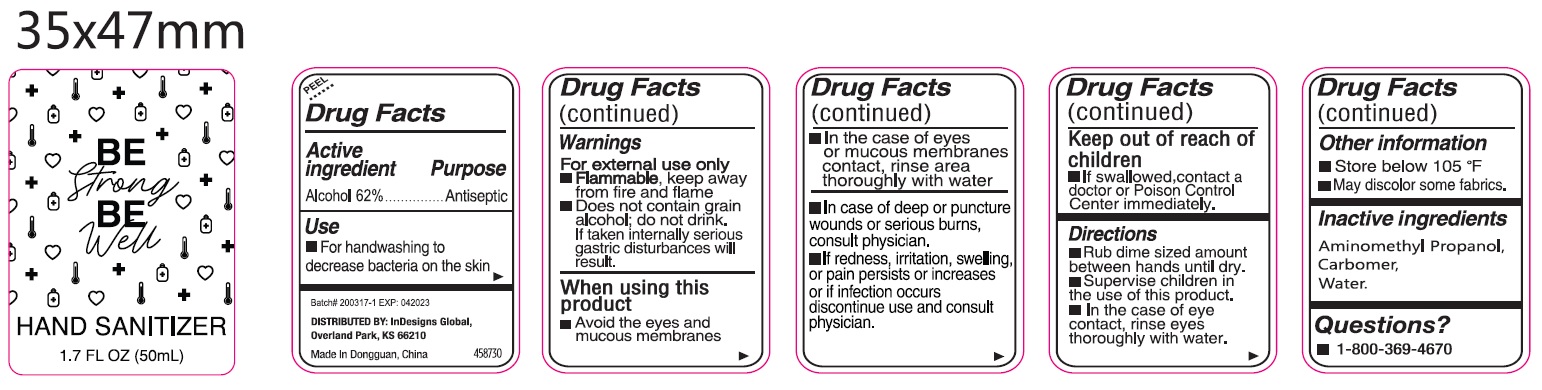 DRUG LABEL: Hand Sanitizer
NDC: 61805-110 | Form: GEL
Manufacturer: Bath Concept Cosmetics (Dongguan) Co., Ltd
Category: otc | Type: HUMAN OTC DRUG LABEL
Date: 20231025

ACTIVE INGREDIENTS: ALCOHOL 0.62 mL/1 mL
INACTIVE INGREDIENTS: AMINOMETHYLPROPANOL; CARBOMER HOMOPOLYMER, UNSPECIFIED TYPE; WATER

Hand Sanitizer

Active Ingredient

Alcohol 62%

Purpose

Antiseptic

Uses

- For handwashing to decrease bacteria on the skin.

Warnings

For external use only.

- , keep away from fire and flame. Flammable
- Does not contain grain alcohol; do not drink, if taken internally serious gastric disturbances will result.

When using this product

- Avoid the eyes and mucous membranes
- In the case of eyes or mucous membranes contact, rinse area thoroughly with water
- In case of deep or puncture wounds or serious burns, consult physician.
- If redness, irritation, swelling or pain persists or increases or if infection occurs discontinue use and consult physician.

KEEP OUT OF REACH OF CHILDREN

- If swallowed, contact a doctor or Poison Control Center immediately.

STOP USE

In case of irritation, discontinue use and consult your doctor.

Directions:

- Rub dime sized amount between hands until dry.
- Supervise children in the use of this product.
- In the case of eye contact, rinse eyes thoroughly with water.

Other Information:

Store below 106ºF (41 ºC). May discolor certain fabrics or surfaces.

Inactive Ingredients

Aminomethyl Propanol, Carbomer, Water.

Questions?

- 1-800-369-4670